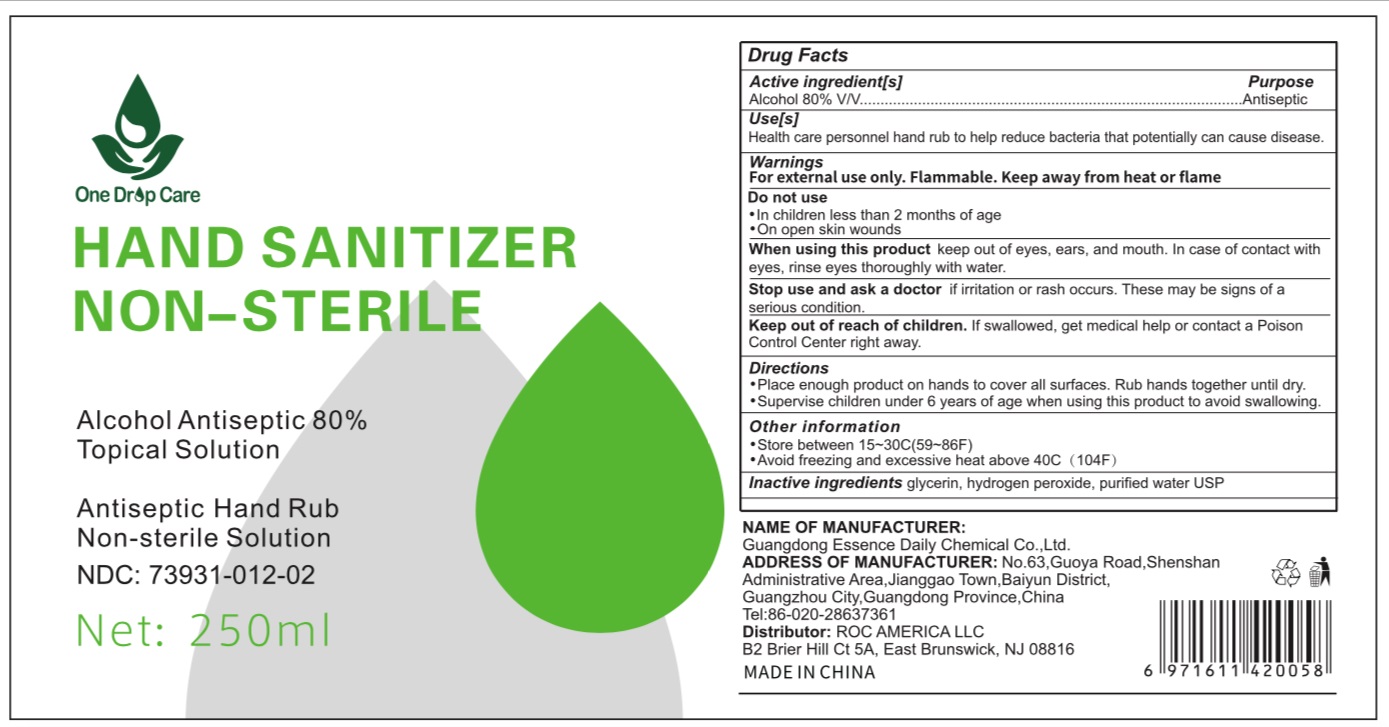 DRUG LABEL: One Drop Care Hand Sanitizer
NDC: 73931-012 | Form: SOLUTION
Manufacturer: Guangdong Essence Daily Chemical Co., Ltd
Category: otc | Type: HUMAN OTC DRUG LABEL
Date: 20200625

ACTIVE INGREDIENTS: ALCOHOL 80 mL/100 mL
INACTIVE INGREDIENTS: WATER; GLYCERIN; HYDROGEN PEROXIDE

Active ingredient

Alcohol 80% (V/V)

Purpose

Antiseptic

Use

health care personnel hand rub to help reduce bacteria that potentially can cause disease.

Warnings

For external use only.

Flammable,

Keep away from heat or flame

Do not use

In children less than 2 months of age

On open skin wounds

When using this product

keep out of eyes, ears, and mout. In case of contact, rinse eyes thoroughly with water.

Stop use and ask a doctor if

irritation or rash occurs. These may be signs of a serious condition.

Keep out of reach of children.

If swallowed, get medical help or contact a Poison Control Center right away.

Inactive ingredients

Glycerin, hydrogen peroxide, purified water USP

Other information

Store between 15-30 ℃（59-86 ℉）

avoid freezing and excessive heat above 40℃ (104℉)